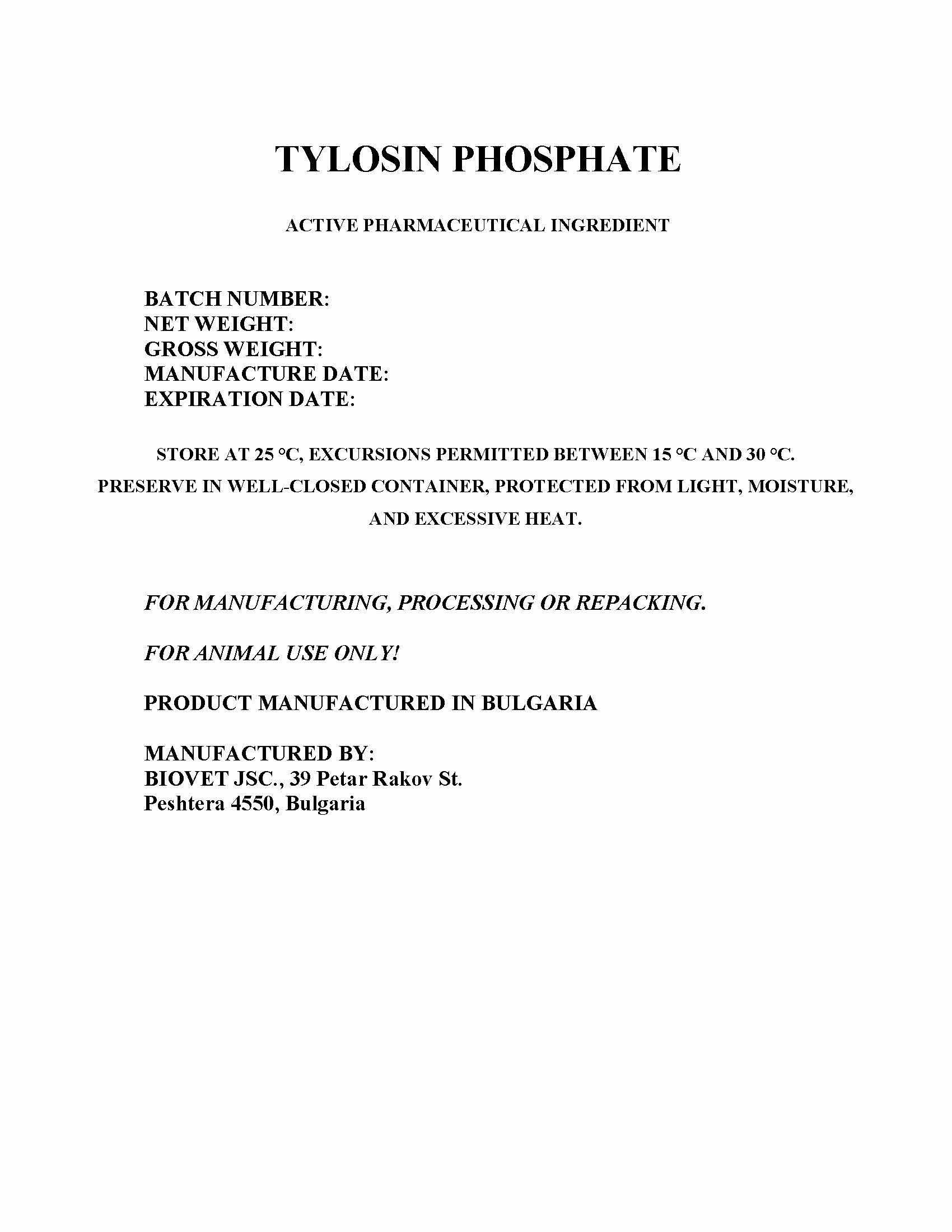 DRUG LABEL: Tylosin Phosphate
NDC: 11311-799 | Form: POWDER
Manufacturer: Biovet Joint Stock Company
Category: other | Type: BULK INGREDIENT - ANIMAL DRUG
Date: 20220112

ACTIVE INGREDIENTS: TYLOSIN PHOSPHATE 1 kg/1 kg

TYLOSIN PHOSPHATE

DRUM LABEL

TYLOSIN PHOSPHATE

ACTIVE PHARMACEUTICAL INGREDIENT

BATCH No:

NET WEIGHT:

GROSS WEIGHT:
MANUFACTURE DATE:
EXPIRATION DATE:

STORE AT OR BELOW 25°C, EXCURSIONS PERMITTED BEWTWEEN 15°C and 30°C.
PRESERVE IN WELL-CLOSED CONTAINER, PROTECTED FROM LIGHT, MOISTURE,

AND EXCESSIVE HEAT.

FOR MANUFACTURING, PROCESSING OR REPACKING.

FOR ANIMAL USE ONLY!

PRODUCT MANUFACTURED IN BULGARIA

MANUFACTURED BY:
BIOVET JSC., 39 Petar Rakov St.,

Peshtera 4550, Bulgaria